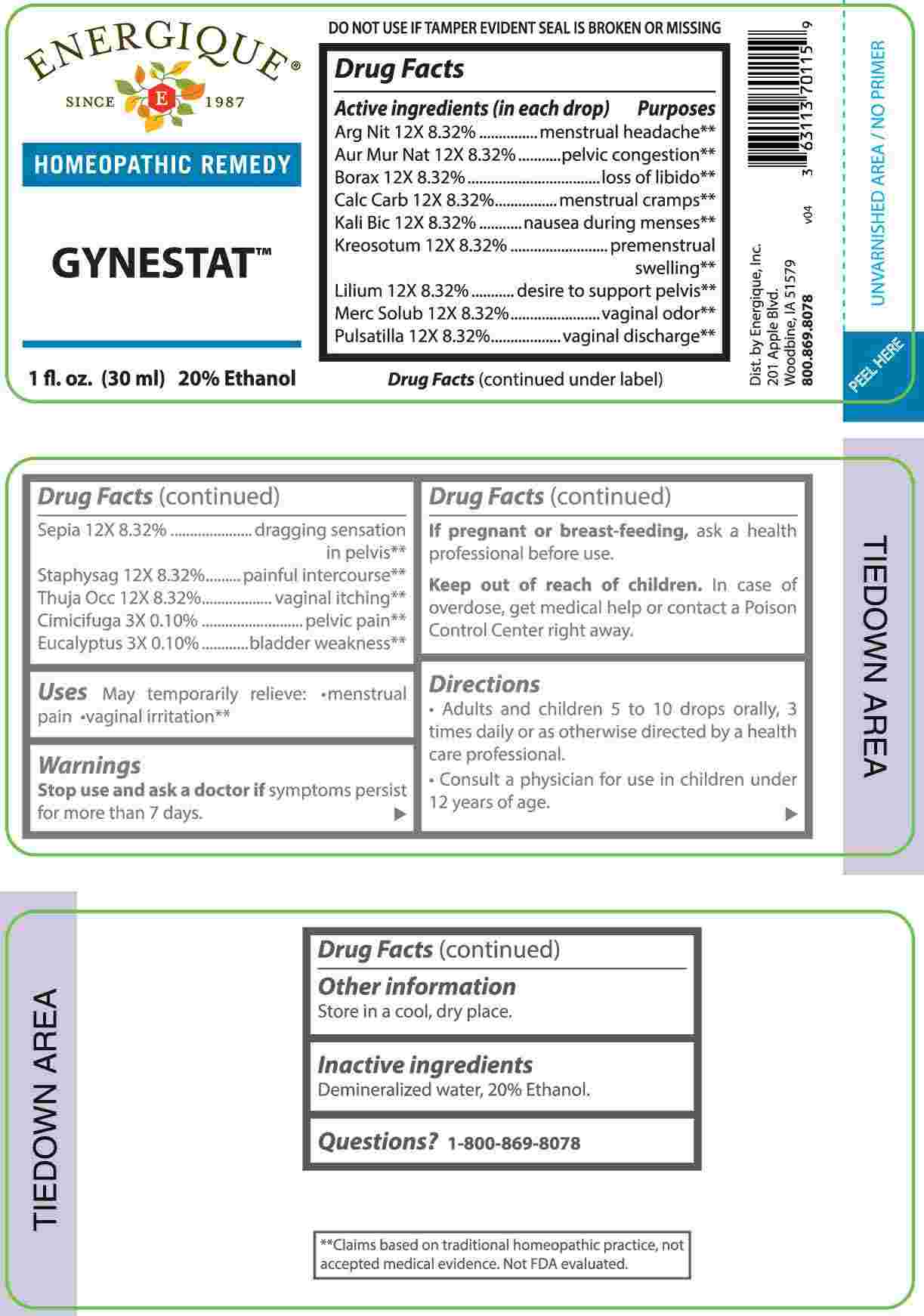 DRUG LABEL: Gynestat
NDC: 44911-0716 | Form: LIQUID
Manufacturer: Energique, Inc.
Category: homeopathic | Type: HUMAN OTC DRUG LABEL
Date: 20240802

ACTIVE INGREDIENTS: BLACK COHOSH 3 [hp_X]/1 mL; EUCALYPTUS GLOBULUS LEAF 3 [hp_X]/1 mL; SILVER NITRATE 12 [hp_X]/1 mL; SODIUM TETRACHLOROAURATE 12 [hp_X]/1 mL; SODIUM BORATE 12 [hp_X]/1 mL; OYSTER SHELL CALCIUM CARBONATE, CRUDE 12 [hp_X]/1 mL; POTASSIUM DICHROMATE 12 [hp_X]/1 mL; WOOD CREOSOTE 12 [hp_X]/1 mL; LILIUM LANCIFOLIUM WHOLE FLOWERING 12 [hp_X]/1 mL; MERCURIUS SOLUBILIS 12 [hp_X]/1 mL; PULSATILLA PRATENSIS WHOLE 12 [hp_X]/1 mL; SEPIA OFFICINALIS JUICE 12 [hp_X]/1 mL; DELPHINIUM STAPHISAGRIA SEED 12 [hp_X]/1 mL; THUJA OCCIDENTALIS LEAFY TWIG 12 [hp_X]/1 mL
INACTIVE INGREDIENTS: WATER; ALCOHOL

DRUG FACTS:

ACTIVE INGREDIENTS:

(in each drop) Argentum Nitricum 12X 8.32%, Aurum Muriaticum Natronatum 12X 8.32%, Borax 12X 8.32%, Calcarea Carbonica 12X 8.32%, Kali Bichromicum 12X 8.32%, Kreosotum 12X 8.32%, Lilium Tigrinum 12X 8.32%, Mercurius Solubilis 12X 8.32%, Pulsatilla 12X 8.32%, Sepia 12X 8.32%, Staphysagria 12X 8.32%, Thuja Occidentalis 12X 8.32%, Cimicifuga Racemosa 3X 0.10%, Eucalyptus Globulus 3X 0.10%

PURPOSE:

Argentum Nitricum – menstrual Headache,** Aurum Muriaticum Natronatum – pelvic congestion,** Borax – loss of libido,** Calcarea Carbonica – menstrual cramps,** Kali Bichromicum – nausea during menses,** Kreosotum – premenstrual swelling,** Lilium Tigrinum – desire to support pelvis,** Mercurius Solubilis – vaginal odor,** Pulsatilla – vaginal discharge,** Sepia – dragging sensation in pelvis,** Staphysagria – painful intercourse,** Thuja Occidentalis – vaginal itching,** Cimicifuga Racemosa – pelvic pain,** Eucalyptus Globulus – bladder weakness**

**Claims based on traditional homeopathic practice, not accepted medical evidence. Not FDA evaluated.

USES:

May temporarily relieve

• menstrual pain • vaginal irritation**

**Claims based on traditional homeopathic practice, not accepted medical evidence. Not FDA evaluated.

WARNINGS:

Stop use and ask a doctor if symptoms persist for more than 7 days.

If pregnant or breast-feeding, ask a health professional before use.

Keep out of reach of children. In case of overdose, get medical help or contact a Poison Control Center right away.

DO NOT USE IF TAMPER EVIDENT SEAL IS BROKEN OR MISSING

Store in a cool, dry place.

KEEP OUT OF REACH OF CHILDREN:

In case of overdose, get medical help or contact a Poison Control Center right away.

DIRECTIONS:

• Adults and children 5 to 10 drops orally, 3 times daily or as otherwise directed by a health care professional.

• Consult a physician for use in children under 12 years of age.

INACTIVE INGREDIENTS:

Demineralized water, 20% Ethanol.

QUESTIONS:

Dist. by Energique, Inc.

201 Apple Blvd

Woodbine, IA 51579

800-869-8078

PACKAGE LABEL DISPLAY:

ENERGIQUE

SINCE 1987

HOMEOPATHIC REMEDY

GYNESTAT

1 fL. oz. (30 ml)